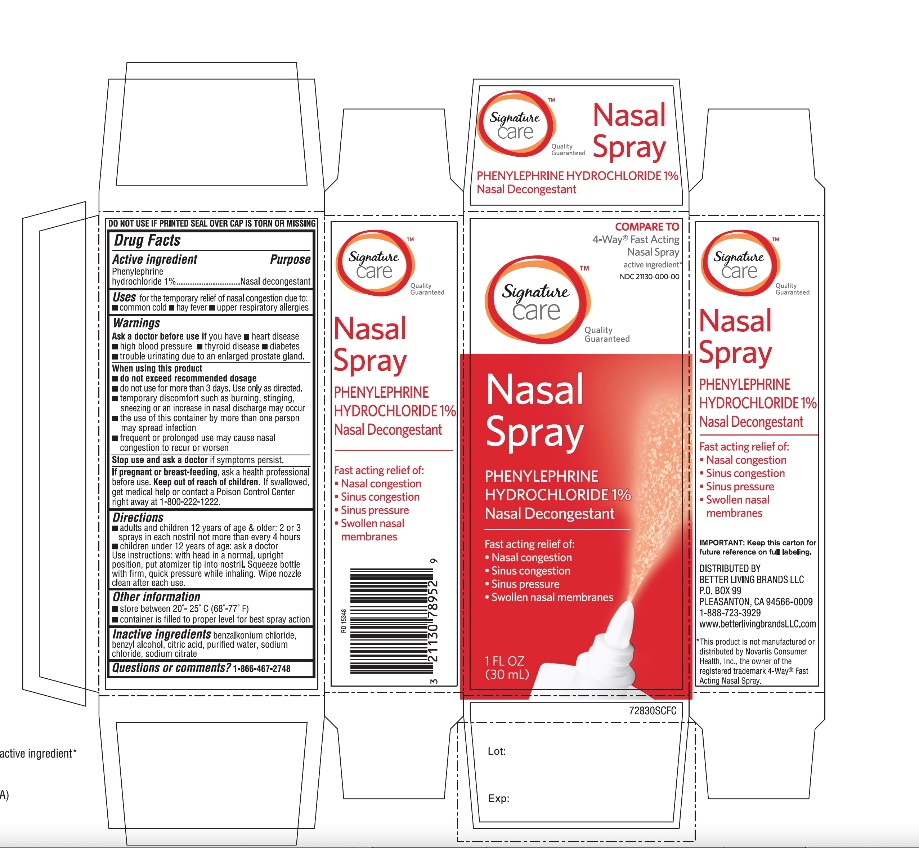 DRUG LABEL: Better Living
NDC: 21130-728 | Form: SPRAY
Manufacturer: BETTER LIVING BRANDS LLC
Category: otc | Type: HUMAN OTC DRUG LABEL
Date: 20251029

ACTIVE INGREDIENTS: PHENYLEPHRINE HYDROCHLORIDE 1 g/100 mL
INACTIVE INGREDIENTS: BENZALKONIUM CHLORIDE; BENZYL ALCOHOL; ANHYDROUS CITRIC ACID; WATER; SODIUM CHLORIDE; SODIUM CITRATE, UNSPECIFIED FORM

Signature Care™Nasal Spray Drug Facts

Active ingredient

Phenylephrine hydrochloride 1%

Purpose

Nasal decongestant

Uses

for the temporary relief of nasal congestion due to:

- common cold
- hay fever
- upper respiratory allergies

Warnings

Ask a doctor before use if you have

- heart disease
- high blood pressure
- thyroid disease
- diabetes
- trouble urinating due to an enlarged prostate gland

When using this product

- do not exceed recommended dosage
- do not use for more than 3 days.
- use only as directed.
- frequent or prolonged use may cause nasal congestion to recur or worsen
- temporary discomfort such as burning, stinging, sneezing or an increase in nasal discharge may occur
- the use of this container by more than one person may spread infection

Stop use and ask a doctor if

symptoms persist.

If pregnant or breast-feeding,

ask a health professional before use.

Keep out of reach of children.

If swallowed, get medical help or contact a Poison Control Center right away at 1-800-222-1222.

Directions

- adults and children 12 years of age & over: 2 or 3sprays in each nostril not more often than every 4 hours
- children under 12 years of age:ask a doctor
- Use instructions: with head in a normal, upright position, put atomizer tip into nostril. Squeeze bottle with firm, quick pressure while inhaling. Wipe nozzle clean after each use.

Other information

- store at room Temperature

Inactive ingredients

benzalkonium chloride, benzyl alcohol, citric acid, purified water, sodium chloride, sodium citrate

Questions or comments?

1-866-467-2748

Principal Display Panel

Compare to the active ingredient in 4-Way Fast Acting Nasal Spray *

NDC 21130-728-30

Signature Care™

Quality Guaranteed

Nasal Spray

Nasal Decongestant

Phenylephrine Hydrochloride

Fast acting relief of:

- Nasal congestion
- Sinus congestion
- Sinus pressure
- Swollen nasal membranes

1 FL OZ (30mL)

DO NOT USE IF PRINTED SEAL OVER CAP IS TORN OR MISSING

Distributed By

IMPORTANT: Keep this carton for future reference on full labeling.

*This product is not manufactured or distributed by GSK Consumer Healthcare, the distributor of 4-Way®Fast acting Nasal Spray.